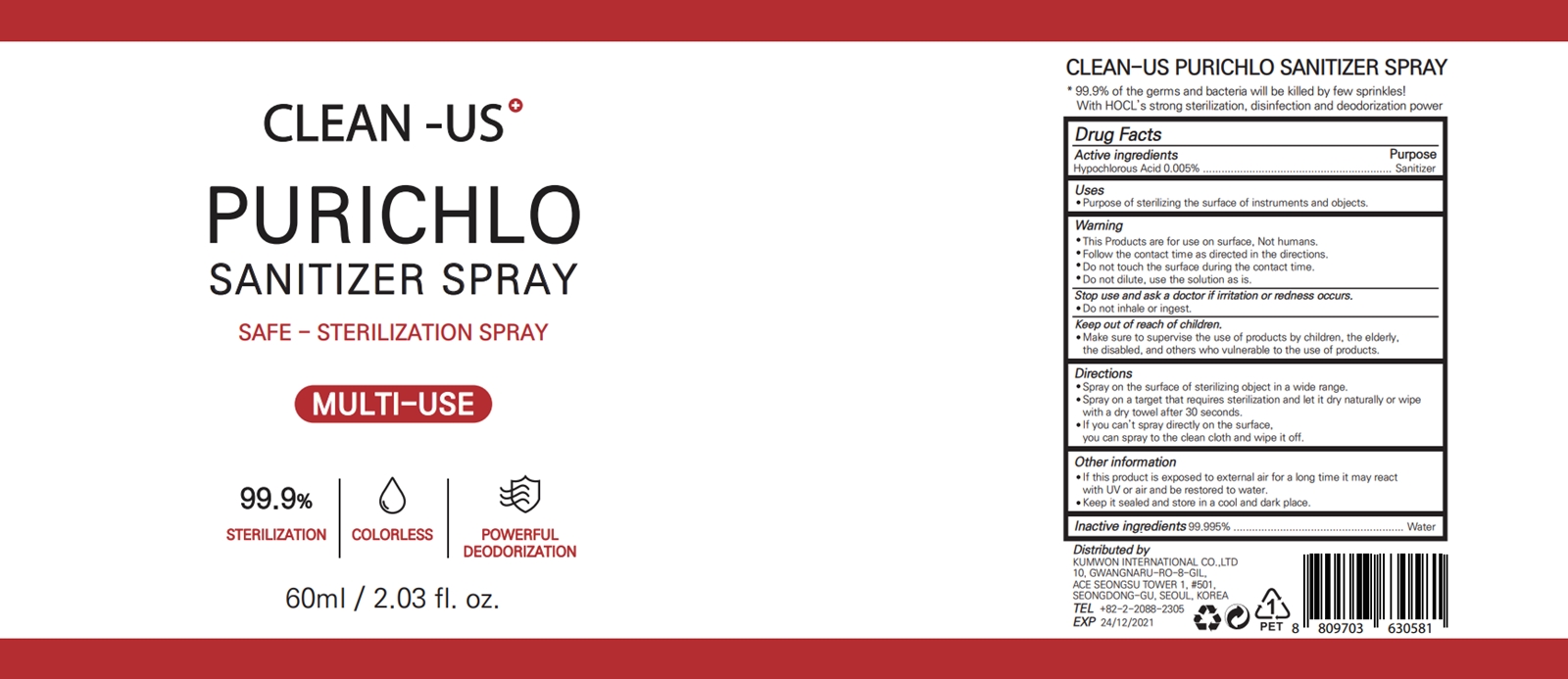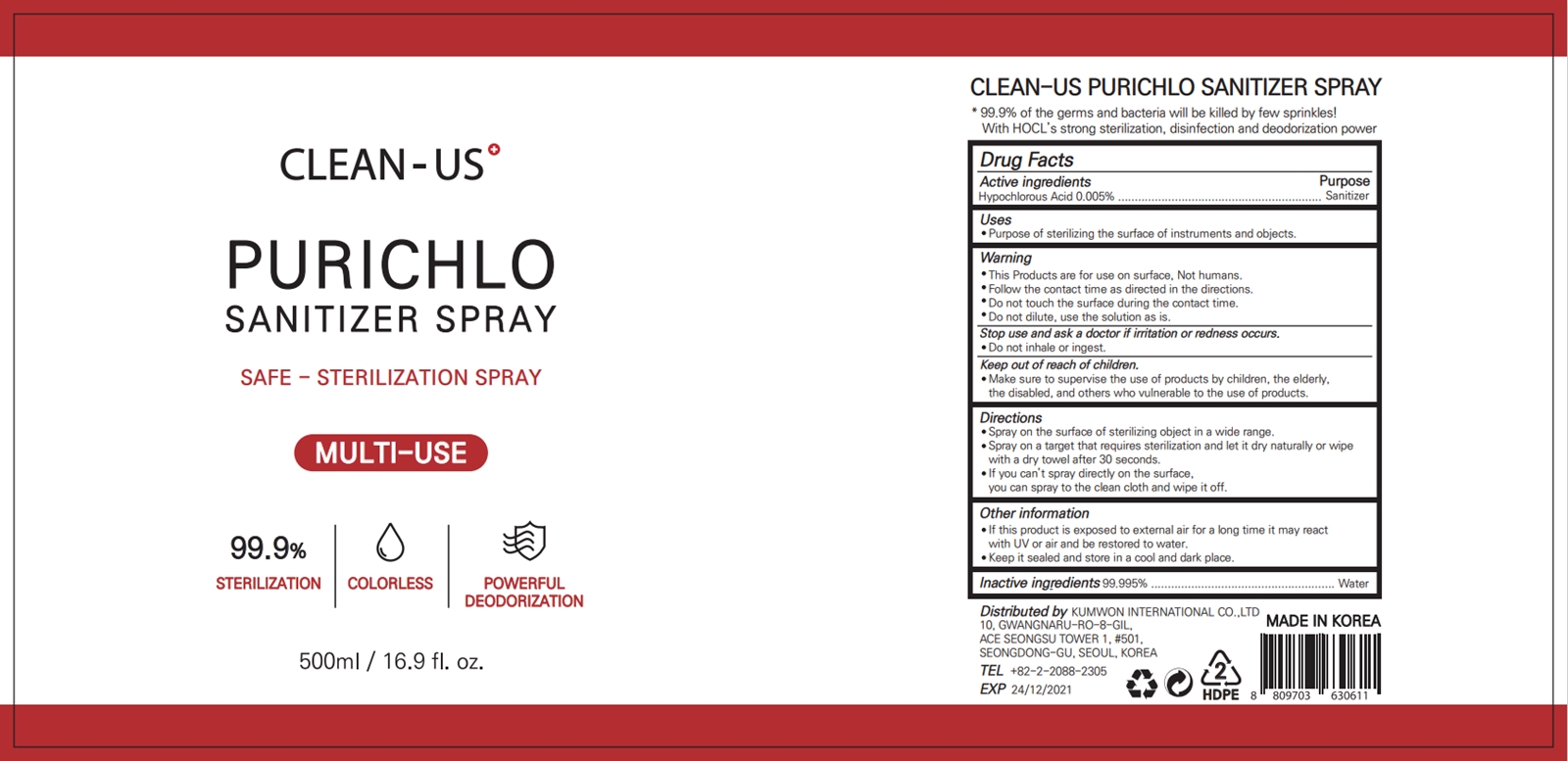 DRUG LABEL: CLEAN-US PURICHLO SANITIZER-Spray
NDC: 79543-201 | Form: LIQUID
Manufacturer: KUMWON INTERNATIONAL INC.
Category: otc | Type: HUMAN OTC DRUG LABEL
Date: 20200922

ACTIVE INGREDIENTS: HYPOCHLOROUS ACID 0.005 g/100 mL
INACTIVE INGREDIENTS: WATER 99.995 mL/100 mL

79543-201

Active ingredients

Hypochlorous Acid 0.005%

Purpose

Sanitizer

Uses

Purpose of sterilizing the surface of instruments and objects.

Warning

This Products are for use on surface, Not humans.

Follow the contact time as directed in the directions.

Do not touch the surface during the contact time.

Do not dilute, use the solution as is.

Stop use and ask a doctor if irritation or redness occurs.

Do not inhale or ingest.

Keep out of reach of children.

Make sure to supervise the use of products by children, the elderly, the disabled, and others who vulnerable to the use of products.

Directions

Spray on the surface of sterilizing object in a wide range.

Spray on a target that requires sterilization and let it dry naturally or wipe with a dry towel after 30 seconds.

If you can’t spray directly on the surface, you can spray to the clean cloth and wipe it off.

Other information

If this product is exposed to external air for a long time it may react with UV or air and be restored to water.

Keep it sealed and store in a cool and dark place.

Inactive ingredients

Water 99.995%